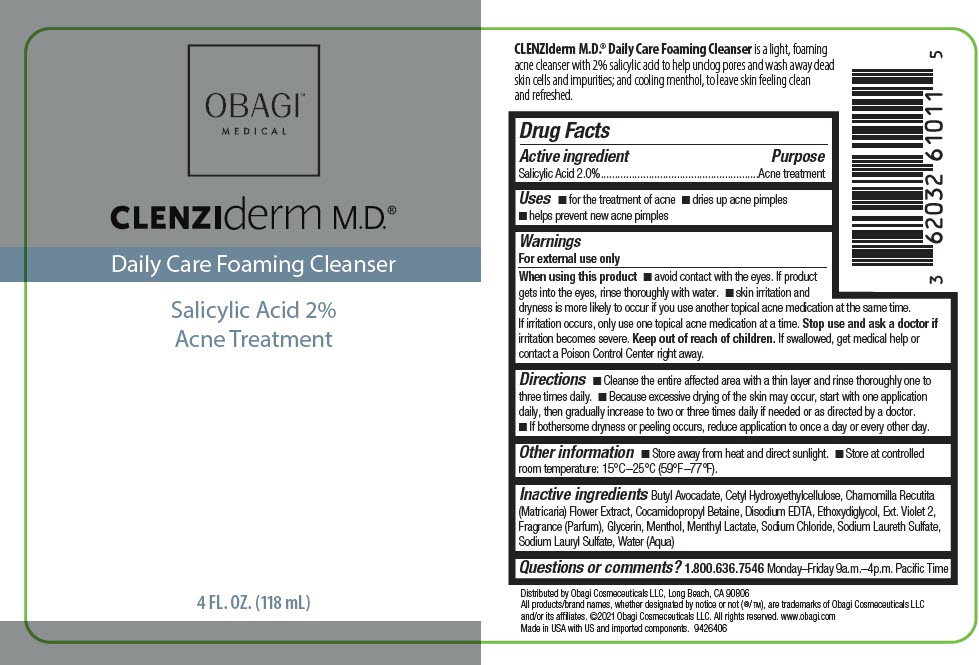 DRUG LABEL: CLENZIDERM DAILY CARE FOAMING CLEANSER
NDC: 62032-610 | Form: LIQUID
Manufacturer: Obagi Cosmeceuticals LLC
Category: otc | Type: HUMAN OTC DRUG LABEL
Date: 20250101

ACTIVE INGREDIENTS: SALICYLIC ACID 20 mg/1 mL
INACTIVE INGREDIENTS: SODIUM LAURETH-3 SULFATE; SODIUM LAURYL SULFATE; COCAMIDOPROPYL BETAINE; CETYL HYDROXYETHYLCELLULOSE (350000 MW); EDETATE DISODIUM; MENTHOL, UNSPECIFIED FORM; MENTHYL LACTATE, (-)-; EXT. D&C VIOLET NO. 2; DIETHYLENE GLYCOL MONOETHYL ETHER; CHAMOMILE; GLYCERIN; WATER; BUTYL AVOCADATE; SODIUM CHLORIDE

CLENZIDERM DAILY CARE FOAMING CLEANSER
ACNE TREATMENT

Drug Facts

Active ingredient

Salicylic Acid 2.0%

Purpose

Acne treatment

Uses

- for the treatment of acne
- dries up acne pimples
- helps prevent new acne pimples

Warnings

For external use only

When using this product

- avoid contact with the eyes. If product gets into the eyes, rinse thoroughly with water.
- skin irritation and dryness is more likely to occur if you use another topical acne medication at the same time. If irritation occurs, only use one topical acne medication at a time.

Stop use and ask a doctor if irritation becomes severe.

Keep out of reach of children. If swallowed, get medical help or contact a Poison Control Center right away.

Directions

- Cleanse the entire affected area with a thin layer and rinse thoroughly one to three times daily.
- Because excessive drying of the skin may occur, start with one application daily, then gradually increase to two or three times daily if needed or as directed by a doctor.
- If bothersome dryness or peeling occurs, reduce application to once a day or every other day.

Other information

- Store away from heat and direct sunlight.
- Store at controlled room temperature: 15°C–25°C (59°F–77°F).

Inactive ingredients

Butyl Avocadate, Cetyl Hydroxyethylcellulose, Chamomilla Recutita (Matricaria) Flower Extract, Cocamidopropyl Betaine, Disodium EDTA, Ethoxydiglycol, Ext. Violet 2, Fragrance (Parfum), Glycerin, Menthol, Menthyl Lactate, Sodium Chloride, Sodium Laureth Sulfate, Sodium Lauryl Sulfate, Water (Aqua)

Questions or comments?

1.800.636.7546 Monday–Friday 9a.m.–4p.m. Pacific Time

Distributed by Obagi Cosmeceuticals LLC, Long Beach, CA 90806

PRINCIPAL DISPLAY PANEL - 118 mL Bottle Label

OBAGI™
MEDICAL

CLENZIderm M.D.®

Daily Care Foaming Cleanser

Salicylic Acid 2%
Acne Treatment

4 FL. OZ. (118 mL)